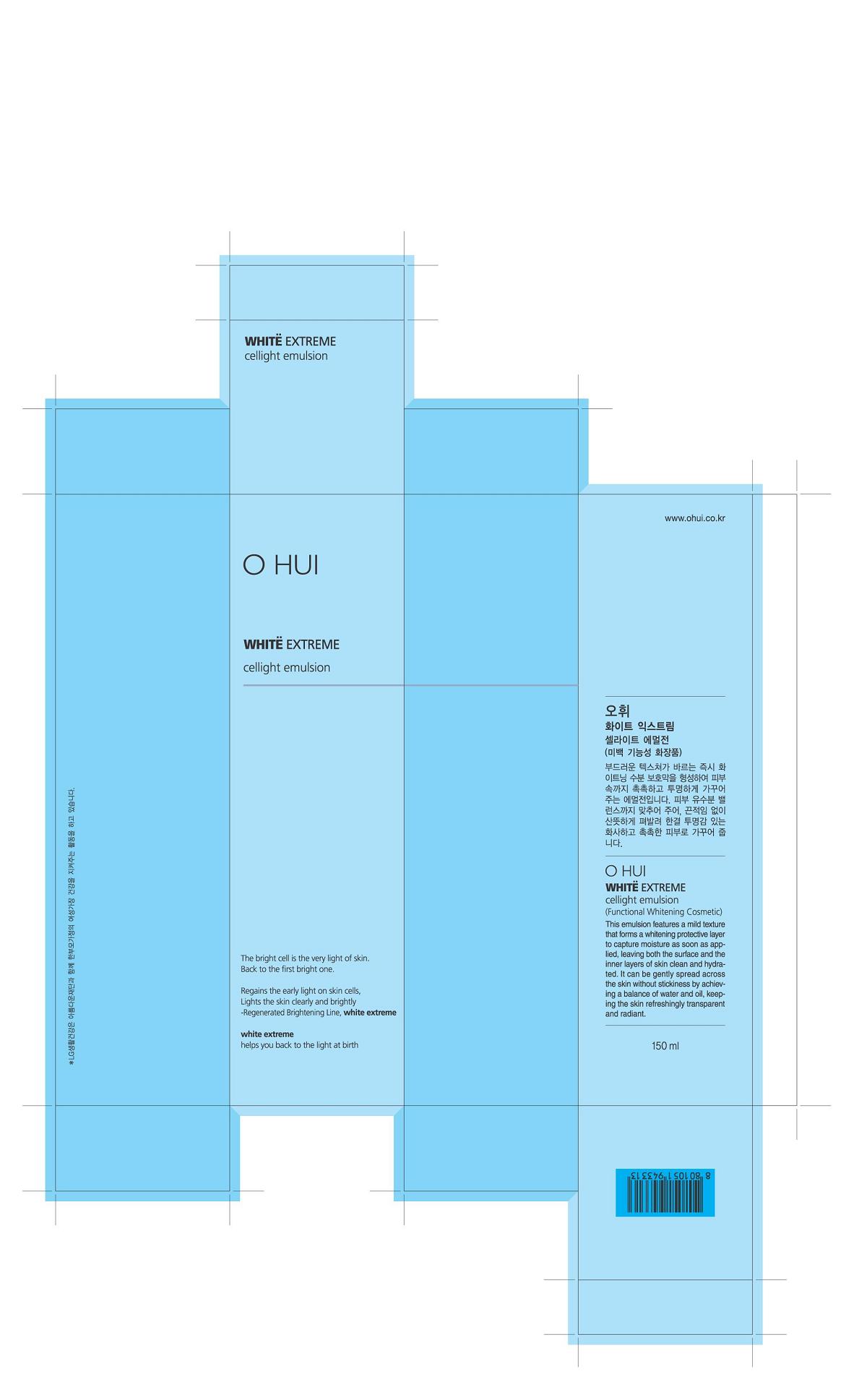 DRUG LABEL: O HUI WHITE EXTREME CELLIGHT
NDC: 53208-501 | Form: EMULSION
Manufacturer: LG Household and Healthcare, Inc.
Category: otc | Type: HUMAN OTC DRUG LABEL
Date: 20120514

ACTIVE INGREDIENTS: PROTOCATECHUALDEHYDE 0.0315 mL/100 mL
INACTIVE INGREDIENTS: WATER; GLYCERIN; DIPROPYLENE GLYCOL; MEDIUM-CHAIN TRIGLYCERIDES; TRIETHYLHEXANOIN; CYCLOMETHICONE 5; GLYCERYL MONOSTEARATE; BIOSACCHARIDE GUM-1; ALCOHOL; PROPYLPARABEN; ETHYLPARABEN; FRUIT; YELLOW WAX; STEARIC ACID; METHYLPARABEN; BETAINE; PANTHENOL; COPPER; XANTHAN GUM; SODIUM METABISULFITE; EDETATE TRISODIUM; CITRIC ACID MONOHYDRATE

Drug Fact

ACTIVE INGREDIENT

PROTOCATECHUALDEHYDE 0.0315%

PURPOSE

Whitening Emulsion

Stop use if rash or irritation develops and lasts.

WHEN USING

Keep out of eyes. Rinse with water to remove.

INDICATIONS AND USAGE

Use to whiten skin.

Keep out of reach of children. Is swallowed, get medical help or contact a Poison Control Center right away.

INACTIVE INGREDIENT

WATER, GLYCERIN, DIPROPYLENE GLYCOL, MEDIUM-CHAIN TRIGLYCERIDES, TRIETHYLHEXANOIN, HYDROGENATED POLYDECENE, CYCLOPENTASILOXANE, BETAINE, BIOSACCHARIDE GUM-1, ALCOHOL, GLYCERYL MONOSTEARATE, FRUIT, YELLOW WAX, STEARIC ACID, PANTHENOL, COPPER TRIPEPTIDE-1, METHYLPARABEN, PROPYLPARABEN, ETHYLPARABEN, XANTHAN GUM, SODIUM METABISULFITE, TRISODIUM EDTA, CITRIC ACID.

PACKAGE LABEL

OHUI
WHITE EXTREME

CELLIGHT EMULSION

DOSAGE AND ADMINISTRATION

Use as needed to whiten skin.